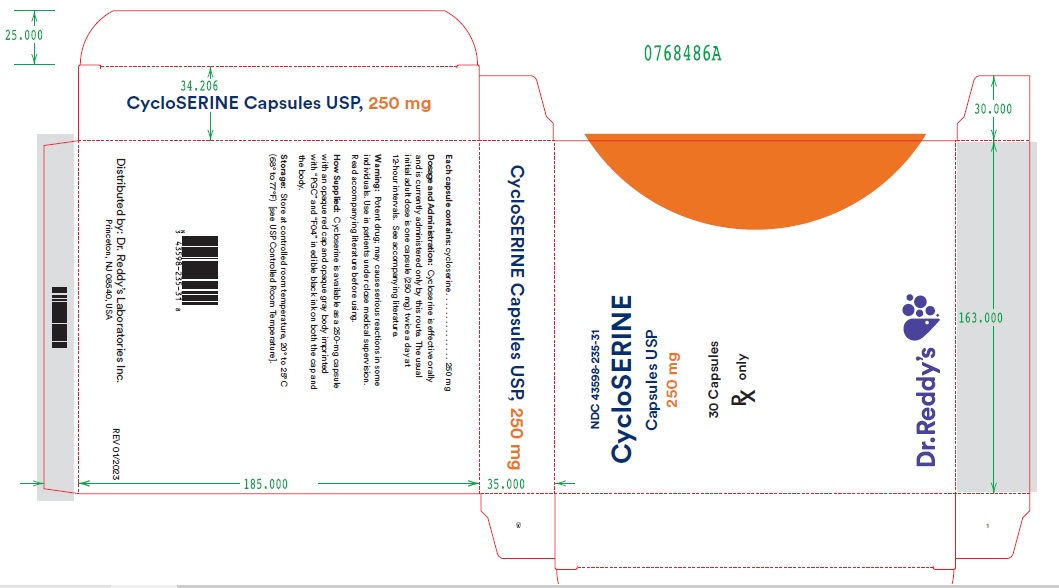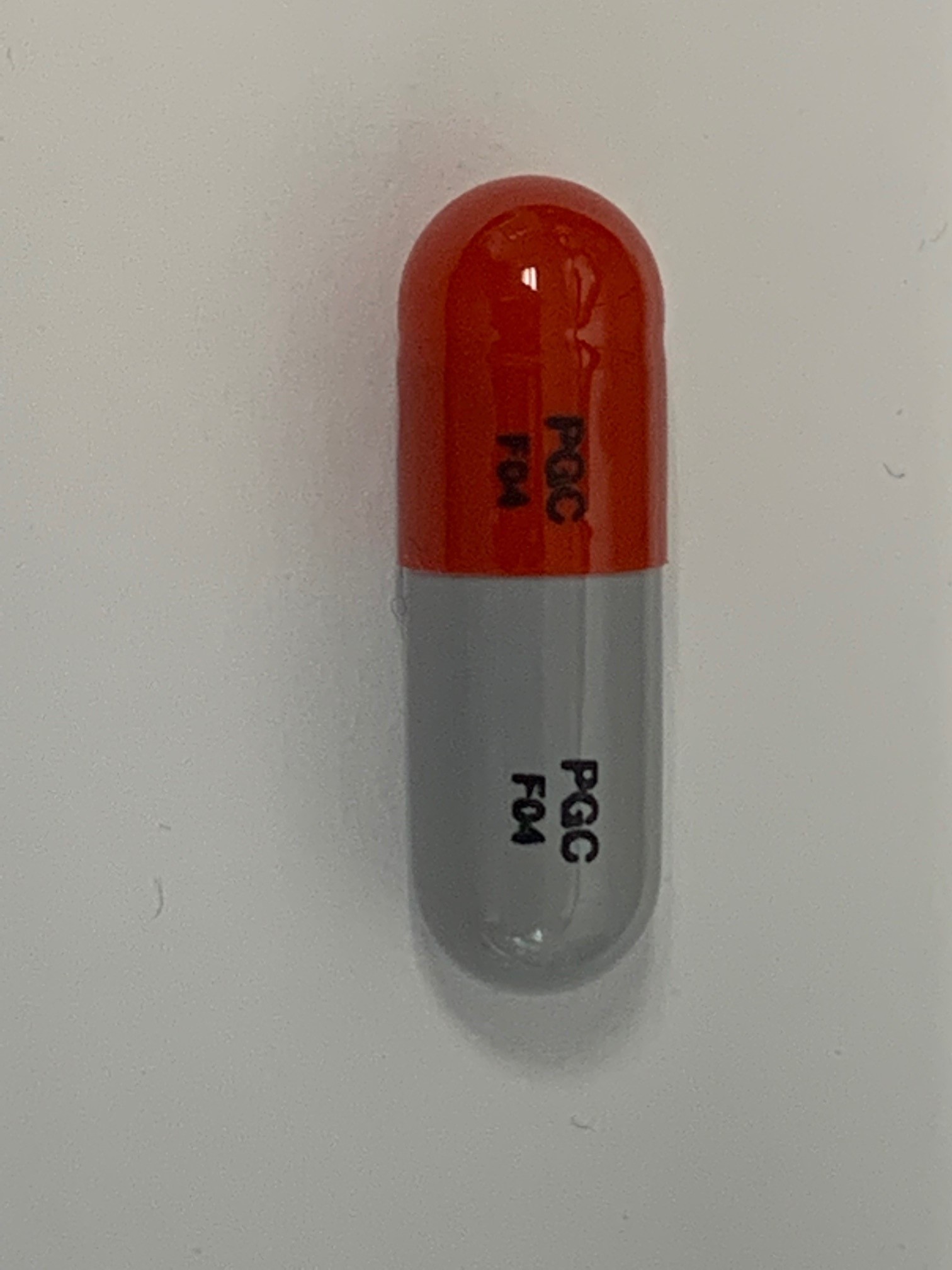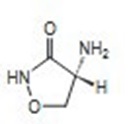 DRUG LABEL: Cycloserine
NDC: 43598-235 | Form: CAPSULE
Manufacturer: Dr. Reddy’s Laboratories, Inc.
Category: prescription | Type: HUMAN PRESCRIPTION DRUG LABEL
Date: 20240730

ACTIVE INGREDIENTS: CYCLOSERINE 250 mg/1 1

Cycloserine Capsules USP, 250 mg

DESCRIPTION

D -Cycloserine, (R)-4-amino-3-isoxazolidinone,
is a broad-spectrum antibiotic that is produced
by a strain of Streptomyces orchidaceus and has
also been synthesized. Cycloserine is a white
to off-white powder that is soluble in water and
stable in alkaline solution. It is rapidly destroyed
at a neutral or acid pH.

Cycloserine has a pH between 5.5 and 6.5 in a
solution containing 100 mg/mL. The molecular
weight of cycloserine is 102.09, and it has an
empirical formula of C 3H6N2O 2 . The structural
formula of cycloserine is as follows:

Each capsule contains cycloserine, 250 mg
(2.45 mmol); D & C Yellow No. 10, F D & C Blue
No. 1, F D & C Red No. 3, F D & C Yellow No.
6, gelatin, iron oxide, talc, and titanium dioxide.

CLINICAL PHARMACOLOGY

After oral administration, cycloserine is
readily absorbed from the gastrointestinal
tract, with peak blood levels occurring in 4
to 8 hours. Blood levels of 25 to 30 mcg/mL
can generally be maintained with the usual
dosage of 250 mg twice a day, although the
relationship of plasma levels to dosage is
not always consistent. Concentrations in the

cerebrospinal fluid, pleural fluid, fetal blood,

and mother’s milk approach those found in
the serum. Detectable amounts are found

in ascitic fluid, file, sputum, amniotic fluid,

and lung and lymph tissues. Approximately
65% of a single dose of cycloserine can
be recovered in the urine within 72 hours
after oral administration. The remaining
35% is apparently metabolized to unknown
substances. The maximum excretion rate
occurs 2 to 6 hours after administration, with
50% of the drug eliminated in 12 hours.

Mechanism of Action: The antibacterial activity
of Cycloserine results from inhibition of cell-wall
synthesis in susceptible strains of gram-positive
and gram-negative bacteria.

Antibacterial Activity: Cycloserine has been
shown to be active against most isolates of the
following microorganism, both in vitro and in
clinical infections [see Indications and Usage]:
Mycobacterium tuberculosis.

INDICATIONS AND USAGE

Cycloserine is indicated in the treatment
of active pulmonary and extrapulmonary
tuberculosis (including renal disease) when
the causative organisms are susceptible to
this drug and when treatment with the primary
medications (streptomycin, isoniazid, rifampin,
and ethambutol) has proved inadequate. Like
all antituberculosis drugs, cycloserine should be
administered in conjunction with other effective
chemotherapy and not as the sole therapeutic
agent.

Cycloserine may be effective in the treatment
of acute urinary tract infections caused by
susceptible strains of gram-positive and gram-
negative bacteria. Use of cycloserine in these
infections should be considered only when
more conventional therapy has failed and when
the organism has been demonstrated to be
susceptible to the drug

CONTRAINDICATIONS

Administration is contraindicated in patients with
any of the following:

• Hypersensitivity to cycloserine
• Epilepsy
• Depression, severe anxiety, or psychosis
• Severe renal insufficiency
• Excessive concurrent use of alcoho

WARNINGS

Administration of cycloserine should be
discontinued or the dosage reduced if
the patient develops allergic dermatitis or
symptoms of CNS toxicity, such as convulsions,
psychosis, somnolence, depression, confusion,

hyperreflexia, headache, tremor, vertigo
paresis, or dysarthria.

The toxicity of cycloserine is closely related to
excessive blood levels (above 30 mcg/mL), as
determined by high dosage or inadequate renal
clearance. The ratio of toxic dose to effective
dose in tuberculosis is small.

The risk of convulsions is increased in chronic
alcoholics.

Patients should be monitored by hematologic,
renal excretion, blood level, and liver function
studies.

PRECAUTIONS

General: Before treatment with cycloserine
is initiated, cultures should be taken and the
organism’s susceptibility to the drug should
be established. In tuberculous infections,
the organism’s susceptibility to the other
antituberculosis agents in the regimen should
also be demonstrated.

Anticonvulsant drugs or sedatives may be
effective in controlling symptoms of CNS
toxicity, such as convulsions, anxiety, and
tremor. Patients receiving more than 500 mg
of cycloserine daily should be closely observed
for such symptoms. The value of pyridoxine in
preventing CNS toxicity from cycloserine has
not been proved.

Administration of cycloserine and other
antituberculosis drugs has been associated in
a few instances with vitamin B 12 and/or folic-

acid deficiency, megaloblastic anemia, and
sideroblastic anemia. If evidence of anemia
develops during treatment, appropriate studies
and therapy should be instituted.

Laboratory Tests: Blood levels should be
determined at least weekly for patients with
reduced renal function, for individuals receiving
a daily dosage of more than 500 mg, and for
those showing signs and symptoms suggestive
of toxicity. The dosage should be adjusted to
keep the blood level below 30 mcg/mL.

Drug Interactions: Concurrent administration
of ethionamide has been reported to potentiate
neurotoxic side effects.

Alcohol and cycloserine are incompatible,
especially during a regimen calling for large
doses of the latter. Alcohol increases the
possibility and risk of epileptic episodes.

Concurrent administration of isoniazid may
result in increased incidence of CNS effects,
such as dizziness or drowsiness. Dosage
adjustments may be necessary and patients
should be monitored closely for signs of CNS
toxicity.

Carcinogenesis, Mutagenicity, and
Impairment of Fertility: Studies have not
been performed to determine potential for
carcinogenicity. The Ames test and unscheduled
DNA repair test were negative. A study in 2
generations of rats showed no impairment of

fertility relative to controls for the first mating but

somewhat lower fertility in the second mating.

Pregnancy Category C: There are no
adequate and well-controlled studies with
the use of Cycloserine in pregnant women.
A study in 2 generations of rats given doses
up to 100 mg/kg/day (approximately equivalent
to the maximum recommended human dose
on a body surface area basis) demonstrated
no teratogenic effect in offspring. Cycloserine
should be used during pregnancy only if the

potential benefit justifies the potential risk to the
fetus.

Nursing Mothers: Because of the potential
for serious adverse reactions in nursing infants
from cycloserine, a decision should be made
whether to discontinue nursing or to discontinue
the drug, taking into account the importance of
the drug to the mother.

Usage in Pediatric Patients: Safety and
effectiveness in pediatric patients have not been
established.

Geriatric Use: Clinical studies of cycloserine

did not include sufficient numbers of subjects

aged 65 and over to determine whether they
responded differently from younger subjects.
Other reported clinical experience has not

identified differences in responses between

the elderly and younger patients. In general,
dose selection for an elderly patient should be
cautious, usually starting at the low end of the

dosing range, reflecting the greater frequency

of decreased hepatic, renal, or cardiac function,
and of concomitant disease or other drug
therapy.

This drug is known to be substantially excreted
by the kidney, and the risk of toxic reactions
to this drug may be greater in patients with
impaired renal function. Because elderly
patients are more likely to have decreased renal
function, care should be taken in dose selection,
and it may be useful to monitor renal function.
The toxicity of cycloserine is closely related
to excessive blood levels (above 30 mcg/mL)
as determined by high dosage or inadequate
renal clearance (see WARNINGS). Blood
levels should be determined at least weekly
for patients with reduced renal function, for
individuals receiving a daily dosage of more
than 500 mg, and for those showing signs
and symptoms suggestive of toxicity. The
dosage should be adjusted to keep the blood
level below 30 mcg/mL (see PRECAUTIONS,

Laboratory Tests).

ADVERSE REACTIONS

Most adverse reactions occurring during therapy
with cycloserine involve the nervous system or
are manifestations of drug hypersensitivity. The
following side effects have been observed in
patients receiving cycloserine:

Nervous system symptoms (which appear to
be related to higher dosages of the drug, i.e.,
more than 500 mg daily)

• Convulsions
• Drowsiness and somnolence
• Headache
• Tremor
• Dysarthria
• Vertigo

• Confusion and disorientation with loss of
memory
• Psychoses, possibly with suicidal tendencies
• Character changes
• Hyperirritability
• Aggression
• Paresis
• Hyperreflexia
• Paresthesia
• Major & minor (localized) clonic seizures
• Coma

Cardiovascular: Sudden development of
congestive heart failure in patients receiving
1 to 1.5 g of cycloserine daily has been
reported.

Allergy (apparently not related to dosage)

Skin rash

Miscellaneous: Elevated serum transaminase,
especially in patients with preexisting liver
disease

To report SUSPECTED ADVERSE REACTIONS, contact Cerovene, Inc. at 1-833-304-9569 or FDA at 1‑800-FDA-1088 or www.fda.gov/medwatch.

OVERDOSAGE

Signs and Symptoms: Acute toxicity from
cycloserine can occur if more than 1 g is
ingested by an adult. Chronic toxicity from
cycloserine is dose related and can occur if
more than 500 mg is administered daily. The
central nervous system is the most common
organ system involved with toxicity. Toxic effects
may include headache, vertigo, confusion,
drowsiness, hyperirritability, paresthesias,
dysarthria, psychosis paresis, convulsions, and
coma.

Treatment: In adults, many of the neurotoxic
effects of cycloserine can be both treated and
prevented with the administration of 200 to 300 mg
of pyridoxine daily.

Hemodialysis has been shown to remove
cycloserine from the bloodstream. This
procedure should be reserved for patients with
life threatening toxicity that is unresponsive to
less invasive therapy.

DOSAGE AND ADMINISTRATION

Cycloserine is effective orally and is currently
administered only by this route. The usual
dosage is 500 mg to 1 g daily in divided doses
monitored by blood levels.^1 The initial adult
dosage most frequently given is 250 mg twice

daily at 12-hour intervals for the first 2 weeks.
A daily dosage of 1 g should not be exceeded.

HOW SUPPLIED

Cycloserine is available as a 250 mg capsule
with an opaque red cap and opaque gray body
imprinted with “PGC” and “F04” in edible black
ink on both the cap and the body.

Cycloserine Capsules, USP are supplied in cartons of 3 cards. Each card is a ten-capsules blister card as follows:

NDC 43598-235-31: carton with 3 cards.

NDC 43598-235-10 (ten 250mg capsules per card).

Store at controlled room temperature,
20° to 25°C (68° to 77°F) [see USP Controlled
Room Temperature].

REFERENCES

1. Jones LR: Colorimetric determination of
cycloserine, a new antibiotic. Anal Chem
1956;28:39.

Distributed By:

Dr. Reddy’s Laboratories, Inc.

Princeton, NJ 08540

Rev 02/23

PACKAGE LABEL DISPLAY

Cycloserine Capsules USP, 250 mg - Carton Label